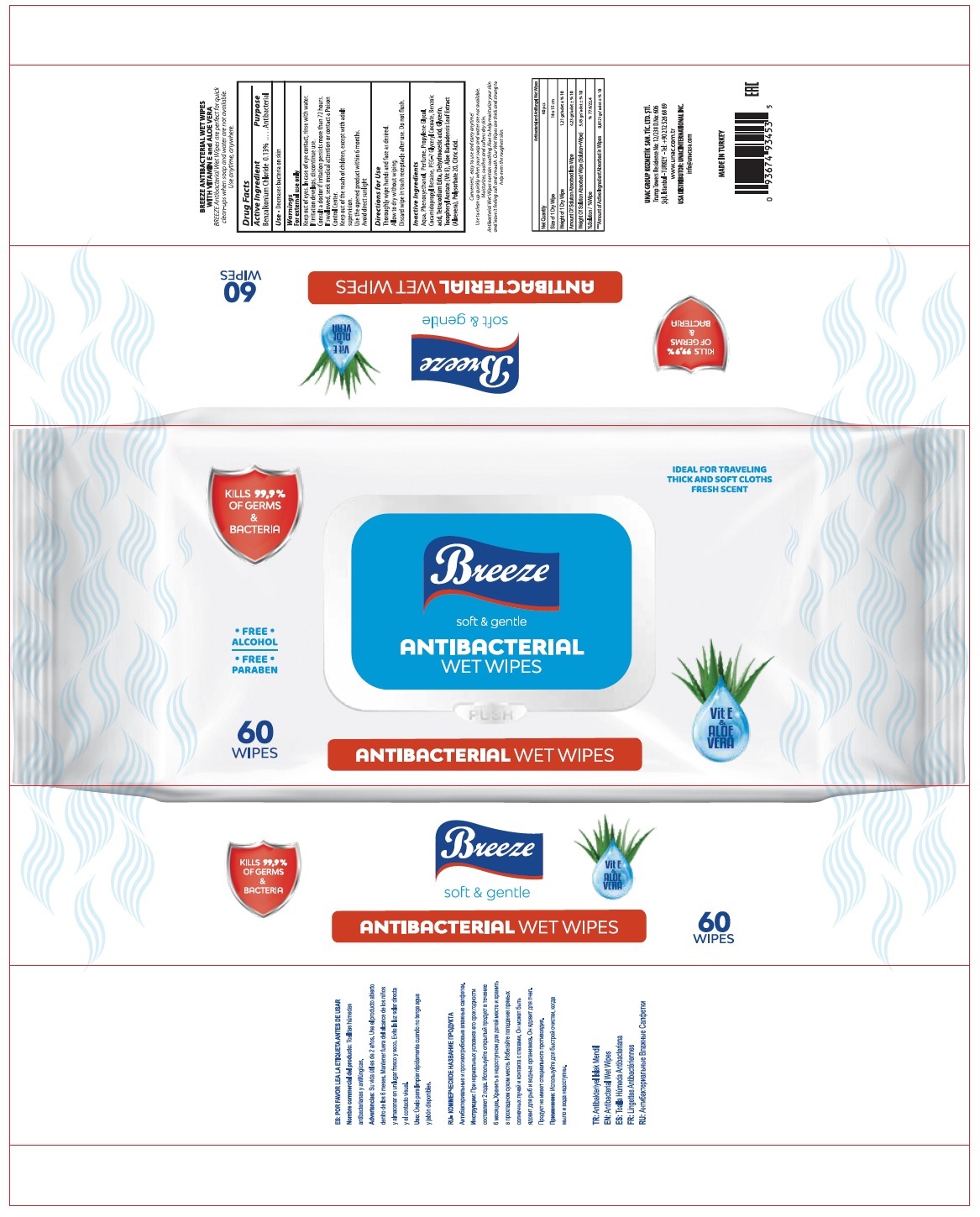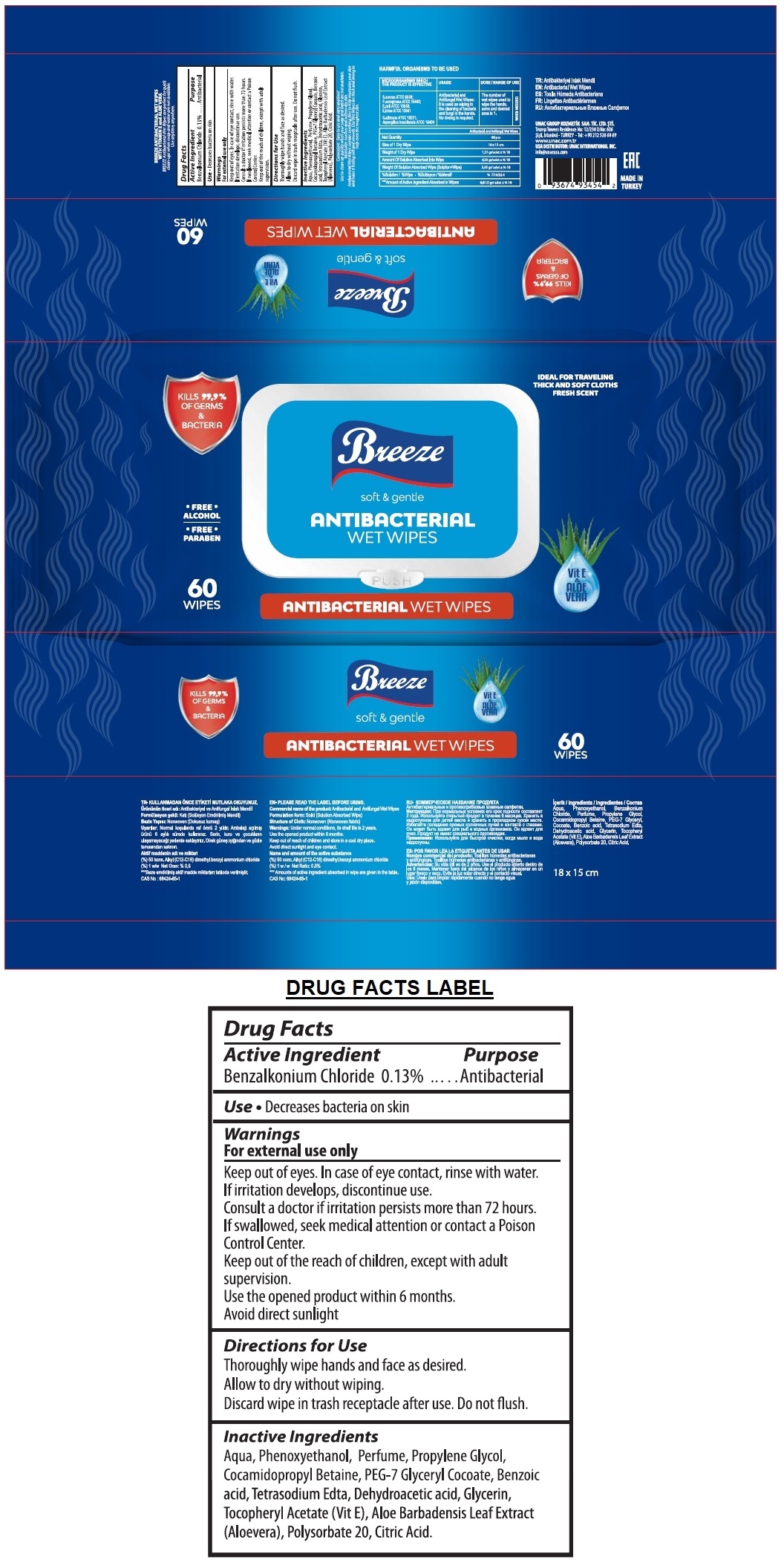 DRUG LABEL: BREEZE ANTIBACTERIAL WET WIPES 60 PCS
NDC: 74955-021 | Form: CLOTH
Manufacturer: COSMOLIVE KOZMETIK SANAYI VE TICARET ANONIM SIRKETI
Category: otc | Type: HUMAN OTC DRUG LABEL
Date: 20200915

ACTIVE INGREDIENTS: BENZALKONIUM CHLORIDE 0.13 g/100 g
INACTIVE INGREDIENTS: WATER; PHENOXYETHANOL; PROPYLENE GLYCOL; COCAMIDOPROPYL BETAINE; PEG-7 GLYCERYL COCOATE; BENZOIC ACID; EDETATE SODIUM; DEHYDROACETIC ACID; GLYCERIN; .ALPHA.-TOCOPHEROL ACETATE; ALOE VERA LEAF; POLYSORBATE 20; CITRIC ACID MONOHYDRATE

BREEZE ANTIBACTERIAL WET WIPES

Active Ingredient

Benzalkonium Chloride 0.13%

Purpose

Antibacterial

INDICATIONS AND USAGE

Use • Decreases bacteria on skin

Warnings

For external use only

Keep out of eyes. In case of eye contact, rinse with water.

If irritation develops, discontinue use.

Consult a doctor if irritation persists more than 72 hours.

Use the opened product within 6 months

Avoid direct sunlight

KEEP OUT OF REACH OF CHILDREN

If swallowed, seek medical attention or contact a Poison Control Center.

Keep out of reach of children, except with adult supervision.

Directions for Use

Thoroughly wipe hands and face as desired.

Allow to dry without wiping.

Discard wipe in trash receptacle after use. Do not flush.

Inactive Ingredients

Aqua, Phenoxyethanol, Perfume, Propylene Glycol, Cocamidopropyl Betaine, PEG-7 Glyceryl Cocoate, Benzoic acid, Tetrasodium Edta, Dehydroacetic acid, Glycerin, Tocopheryl Acetate (Vit E), Aloe Barbadensis Leaf Extract (Aloevera), Polysorbate 20, Citric Acid.

soft & gentle

KILLS 99.9% OF GERMS & BACTERIA

• FREE • ALCOHOL

• FREE • PARABEN

IDEAL FOR TRAVELLING

THICK AND SOFT CLOTHS

FRESH SCENT

Vit E & ALOE VERA

BREEZE ANTIBACTERIAL WET WIPES WITH VITAMIN E and ALOE VERA

BREEZE Antibacterial Wet Wipes are perfect for quick clean-ups when soap and water are not available. Use anytime, anywhere.

Convenient Easy to use and carry anytime!

Use to clean up quickly when your soap and water are not available.

Moisturize Soothes and softens dry skin.

Antibacterial Wet Wipes contain soothing Aloe to help moisturize your skin and leave it feeling soft and smooth. Our Wet Wipes are thick and strong to help even the roughest skin.

Antibacterial and Antifungal Wet Wipes

Net Quantity 60 pcs

Size of 1 Dry Wipe 18 X 15 cms

Weight of 1 Dry Wipe 1,21 gr/adet + %10

Amount of Solution Absorbed Into Wipe 4,23 gr/adet + %10

Weight of Solution Absorbed Wipe (Solution+Wipe) 5,45 gr/adet + %10

%Solution / % Wipe % 77.6/22.4

***Amount of Active Ingredient Absorbed in Wipes 0,0121gr/adet + %10

UNAC GROUP KOZMETIK SAN. TIC. LTD. STI.

Trump Towers Residence No: 12/238 D.No: 606

Sisli, Istanbul - TURKEY -Tel: +90 212 526 68 69

www.unac.com.tr

USA DISTRIBUTOR: UNAC INTERNATIONAL INC.

info@unacusa.com

EAC

MADE IN TURKEY